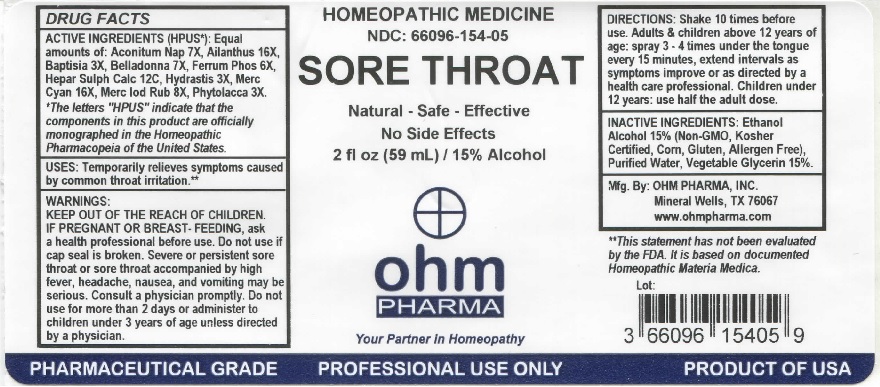 DRUG LABEL: OHM Sore Throat
NDC: 66096-154 | Form: SPRAY
Manufacturer: OHM PHARMA INC.
Category: homeopathic | Type: HUMAN OTC DRUG LABEL
Date: 20211229

ACTIVE INGREDIENTS: ACONITUM NAPELLUS 7 [hp_X]/59 mL; AILANTHUS ALTISSIMA FLOWERING TWIG 16 [hp_X]/59 mL; BAPTISIA TINCTORIA 3 [hp_X]/59 mL; ATROPA BELLADONNA 7 [hp_X]/59 mL; FERROSOFERRIC PHOSPHATE 6 [hp_X]/59 mL; CALCIUM SULFIDE 12 [hp_C]/59 mL; GOLDENSEAL 3 [hp_X]/59 mL; MERCURIC CYANIDE 16 [hp_X]/59 mL; MERCURIC IODIDE 8 [hp_X]/59 mL; PHYTOLACCA AMERICANA ROOT 3 [hp_X]/59 mL
INACTIVE INGREDIENTS: ALCOHOL; WATER; GLYCERIN

OHM Sore Throat

ACTIVE INGREDIENT

ACTIVE INGREDIENTS (HPUS*): Equal amounts of: Aconitum Nap 7X, Ailanthus 16X, Baptisia 3X, Belladonna 7X, Ferrum Phos 6X, Hepar Sulph Calc 12C, Hydrastis 3X, Merc Cyan 16X, Merc Iod Rub 8X, Phytolacca 3X.

*The letters "HPUS" indicate that the components in this product are officially monographed in the Homeopathic Pharmacopeia of the United States.

INDICATIONS AND USAGE

USES: Temporarily relieves symptoms caused by common throat irritation.**

**This statement has not been evaluated by the FDA. It is based on documented Homeopathic Materia Medica.

WARNINGS

WARNINGS: IF PREGNANT OR BREAST-FEEDING, ask a health professional before use. Severe or persistent sore throat or sore throat accompanied by high fever, headache, nausea, and vomitting may be serious. Consult a physician promptly. Do not use for more than 2 days or administer to children under 3 years of age unless directed by a physician.

- KEEP OUT OF REACH OF CHILDREN.

DOSAGE AND ADMINISTRATION

DIRECTIONS: Shake 10 times before use. Adults & children above 12 years of age: spray 3-4 times under the tongue every 15 minutes, extend intervals as symptoms improve or as directed by a health care professional. Children under 12 years: use half the adult dose.

Do not use if cap seal is broken.

INACTIVE INGREDIENT

INACTIVE INGREDIENTS: Ethanol Alcohol 15% (Non-GMO, Kosher Certified, Corn, Gluten, Allergen Free), Purified Water, Vegetable Glycerin 15%.

QUESTIONS

Mfg. By: OHM PHARMA, INC. Mineral Wells, TX 76067

www.ohmpharma.com

PACKAGE LABEL

HOMEOPATHIC MEDICINE

NDC: 66096-154-05

SORE THROAT

Natural - Safe - Effective

No Side Effects

2 fl oz (59 mL) / 15% Alcohol

Product of USA

PURPOSE

Relief from sore throat.